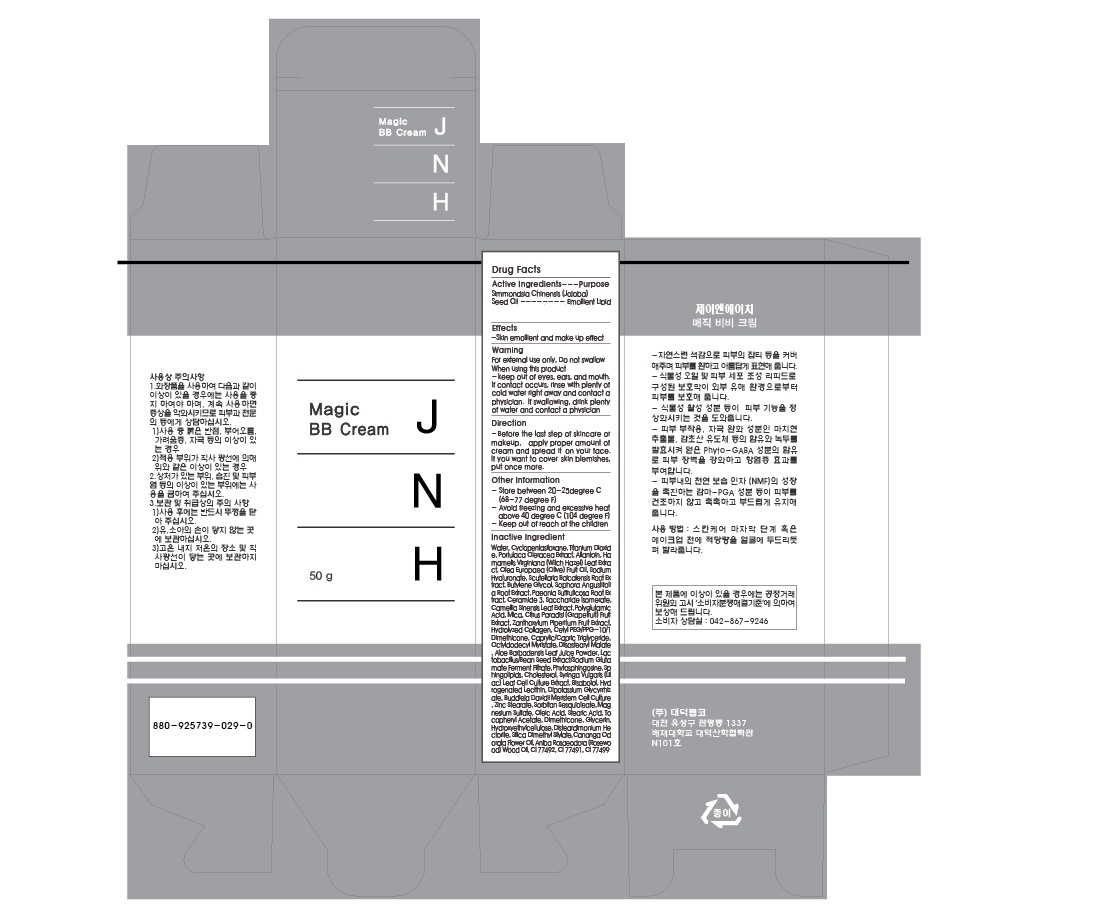 DRUG LABEL: JNH Magic BB
NDC: 53010-2001 | Form: CREAM
Manufacturer: Daeduck Lab Co., Ltd
Category: otc | Type: HUMAN OTC DRUG LABEL
Date: 20120824

ACTIVE INGREDIENTS: SIMMONDSIA CHINENSIS SEED 0.9 g/30 g
INACTIVE INGREDIENTS: WHEAT GERM; CYCLOMETHICONE 5; TITANIUM DIOXIDE; PORTULACA OLERACEA WHOLE; ALLANTOIN; HAMAMELIS VIRGINIANA LEAF; OLEA EUROPAEA FRUIT VOLATILE OIL; HYALURONATE SODIUM; SCUTELLARIA BAICALENSIS ROOT; BUTYLENE GLYCOL; SOPHORA FLAVESCENS ROOT; PAEONIA SUFFRUTICOSA ROOT; CERAMIDE 3; SACCHARIDE ISOMERATE; TEA LEAF OIL; MICA; CITRUS PARADISI FRUIT OIL; ZANTHOXYLUM PIPERITUM FRUIT PULP; HYDROLYSED BOVINE COLLAGEN (ENZYMATIC; 2000-5000 MW); CETYL PEG/PPG-10/1 DIMETHICONE (HLB 1.5); MEDIUM-CHAIN TRIGLYCERIDES; OCTYLDODECYL MYRISTATE; DIISOSTEARYL MALATE; ALOE VERA LEAF; LIMA BEAN; MONOSODIUM GLUTAMATE; PHYTOSPHINGOSINE; CHOLESTEROL; SYRINGA VULGARIS FLOWER; LEVOMENOL; HYDROGENATED SOYBEAN LECITHIN; GLYCYRRHIZINATE DIPOTASSIUM; BUDDLEJA DAVIDII WHOLE; ZINC STEARATE; SORBITAN SESQUIOLEATE; MAGNESIUM SULFATE; OLEIC ACID; STEARIC ACID; .ALPHA.-TOCOPHEROL ACETATE; DIMETHICONE; GLYCERIN; SILICA DIMETHYL SILYLATE; CANANGA ODORATA FLOWER; ROSEWOOD OIL; FERRIC OXIDE YELLOW; FERRIC OXIDE RED; FERROSOFERRIC OXIDE

Drug Facts

ACTIVE INGREDIENT

simmondsia chinensis seed oil

INACTIVE INGREDIENT

- Water - Caprylic/Capric Triglyceride - Butylene Glycol - PEG-10 Dimethicone - Silica - Portulaca Oleracea Extract - - Water - Cyclopentasiloxane - Titanium Dioxide - Portulaca Oleracea Extract - Allantoin - Hamamelis Virginiana (Witch Hazel) Leaf Extract - Olea Europaea (Olive) Fruit Oil - Sodium Hyaluronate - Scutellaria Baicalensis Root Extract - Butylene Glycol - Sophora Angustifolia Root Extract - Paeonia Suffruticosa Root Extract - Ceramide 3
- Saccharide Isomerate - Camellia Sinensis Leaf Extract - Polyglutamic Acid - Mica - Citrus Paradisi (Grapefruit) Fruit Extract - Zanthoxylum Piperitum Fruit Extract - Hydrolyzed Collagen - Cetyl PEG/PPG-10/1 Dimethicone - Caprylic/Capric Triglyceride - Octyldodecyl Myristate - Diisostearyl Malate - Aloe Barbadensis Leaf Juice Powder
- Lactobacillus/Bean Seed Extract/Sodium Glutamate Ferment Filtrate - Phytosphingosine - Sphingolipids - Cholesterol - Syringa Vulgaris (Lilac) Leaf Cell Culture Extract - Bisabolol - Hydrogenated Lecithin - Dipotassium Glycyrrhizate - Buddleja Davidii Meristem Cell Culture - Zinc Stearate - Sorbitan Sesquioleate - Magnesium Sulfate - Oleic Acid - Stearic Acid - Tocopheryl Acetate - Dimethicone – Glycerin - Hydroxyethylcellulose - Disteardimonium Hectorite - Silica Dimethyl Silylate - Cananga Odorata Flower Oil - Aniba Rosaeodora (Rosewood) Wood Oil - CI 77492 - CI 77491 - CI 77499

PURPOSE

skin emollient and make up effect

keep out of reach of the children

INDICATIONS AND USAGE

- Before the last step of skincare or makeup, apply proper amount of cream and spread it on your face. If you want to cover skin blemishes, put once more

When using this product
- keep out of eyes, ears, and mouth. If contact occurs, rinse with plenty of cold water right away and contact a physician. If swallowing, drink plenty of water and contact a physician

DOSAGE AND ADMINISTRATION

for external use only